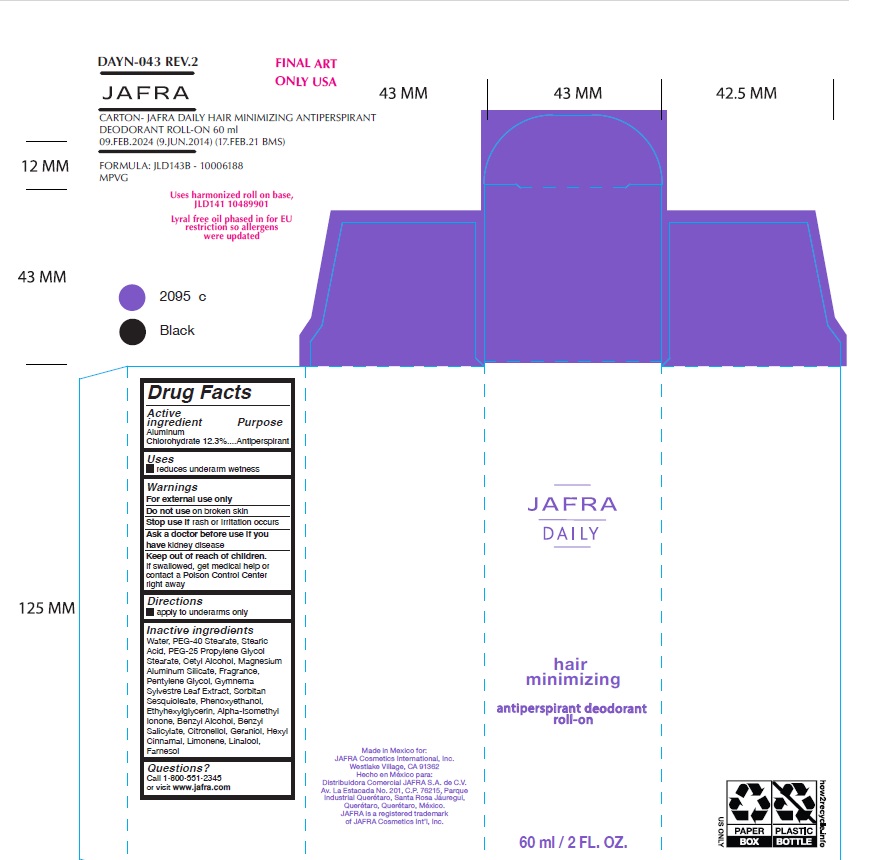 DRUG LABEL: Jafra Daily Hair Minimizing Antiperspirant Deodorant Roll-on
NDC: 68828-703 | Form: LIQUID
Manufacturer: Distribuidora Comercial Jafra, S.A. de C.V.
Category: otc | Type: HUMAN OTC DRUG LABEL
Date: 20250102

ACTIVE INGREDIENTS: ALUMINUM CHLOROHYDRATE 12.3 g/100 mL
INACTIVE INGREDIENTS: WATER; PEG-40 MONOSTEARATE; PEG-25 PROPYLENE GLYCOL STEARATE; STEARIC ACID; CETYL ALCOHOL; MAGNESIUM ALUMINUM SILICATE; PENTYLENE GLYCOL; GYMNEMA SYLVESTRE LEAF; ISOMETHYL-.ALPHA.-IONONE; BENZYL ALCOHOL; BENZYL SALICYLATE; .BETA.-CITRONELLOL, (R)-; GERANIOL; .ALPHA.-HEXYLCINNAMALDEHYDE; LIMONENE, (+)-; LINALOOL, (+/-)-; FARNESOL; SORBITAN SESQUIOLEATE; PHENOXYETHANOL; ETHYLHEXYLGLYCERIN

Jafra Daily Hair Minimizing Antiperspirant Deodorant Roll-on

Active ingredient

Aluminum Chlorohydrate 12.3%

Purpose

Antiperspirant

Uses

- reduces underarm wetness

Warnings

For external use only
Do not use on broken skin
Stop use ifrash or irritation occurs
Ask a doctor before use if youhave kidney disease
Keep out of reach of children. If swallowed, get medical help or contact a Poison Control Center right away.

Directions

- apply to underarms only

Inactive Ingredients

Water, PEG-40 Stearate, Stearic Acid , PEG-25 Propylene Glycol Stearate, Cetyl Alcohol, Magnesium Aluminum Silicate, Fragrance, Pentylene Glycol, Gymnema Sylvestre Leaf Extract, Sorbitan Sesquioleate, Phenoxyethanol, Ethylhexylglycerin, Alpha-Isomethyl Ionone, Benzyl Alcohol, Benzyl Salicylate, Citronellol, Geraniol, Hexyl Cinnamal, Limonene, Linalool, Farnesol

Questions?
Call 1-800-551-2345 or visit www.jafra.com